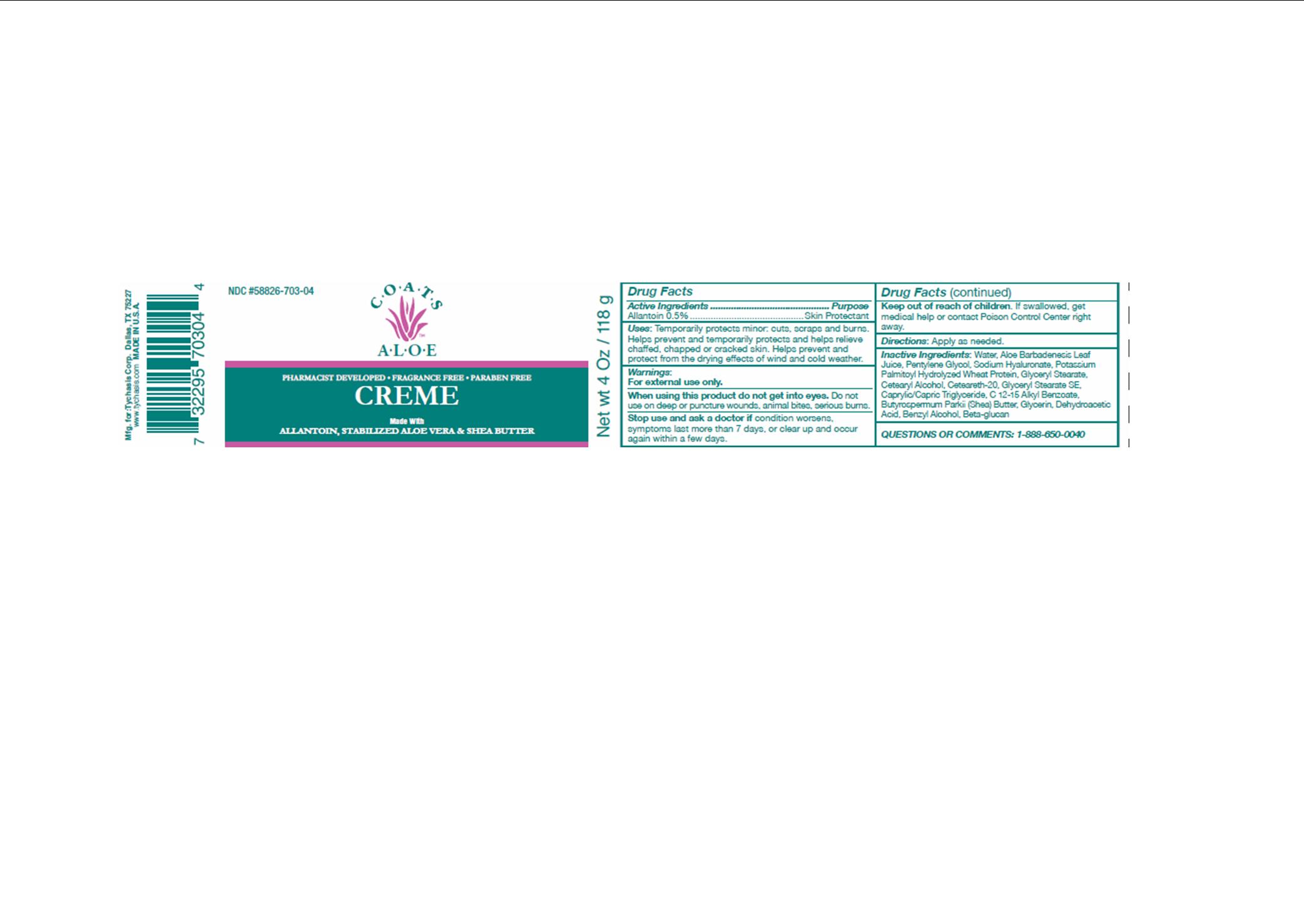 DRUG LABEL: COATS ALOE
NDC: 58826-703 | Form: CREAM
Manufacturer: TYCHASIS CORPORATION
Category: otc | Type: HUMAN OTC DRUG LABEL
Date: 20151009

ACTIVE INGREDIENTS: ALLANTOIN 5 mg/1 g
INACTIVE INGREDIENTS: ALOE VERA LEAF; CAPRYLIC/CAPRIC/LAURIC TRIGLYCERIDE; PENTYLENE GLYCOL; WATER; HYDROLYZED WHEAT PROTEIN (ENZYMATIC, 3000 MW); POTASSIUM PALMITATE; GLYCERYL STEARATE SE; SHEA BUTTER; C12-15 ALKYL BENZOATE; GLYCERIN; HYALURONATE SODIUM; DEHYDROACETIC ACID; BENZYL ALCOHOL

COATS ALOE CREME

Active Ingredient

Allantoin 0.5%

Uses:

Skin protectant

Warnings

For external use only.

Do not get into eyes.

Stop use and ask a doctor if condition worsens, symptoms last more than 7 days, or clear up and occur again within a few days.

Uses:

Temporarily protects minor:

- cuts
- scrapes
- burns

Helps prevent and temporarily protects and helps relieve chaffed, chapped or cracked skin.

Helps prevent and protect from the drying effects of wind and cold weather.

Caution:

Do not use on deep puncture wounds, animal bites, serious burns.

Keep out of reach of children

If swallowed, get medical help or contact a Poison Control Center right away.

Directions:

Apply as needed.

Directions:

Apply as needed.

Inactive Ingredients:

water, aloe barbadensis leaf juice, caprylic/-capric triglyceride, cetyl alcohol, postassium palmitoyl hydrolyzed wheat protein, glycerol stearate, pentylene glycol, butyrospermum parkii (shea) butter, c12-15 alkyl benzoate, glycerin, beta-glucan, sodium hyaluronate, glyceryl stearate SE, cetearath-20, dehydroacetic acid, benzyl alcohol

Questions:

Toll free number 888-650-0040